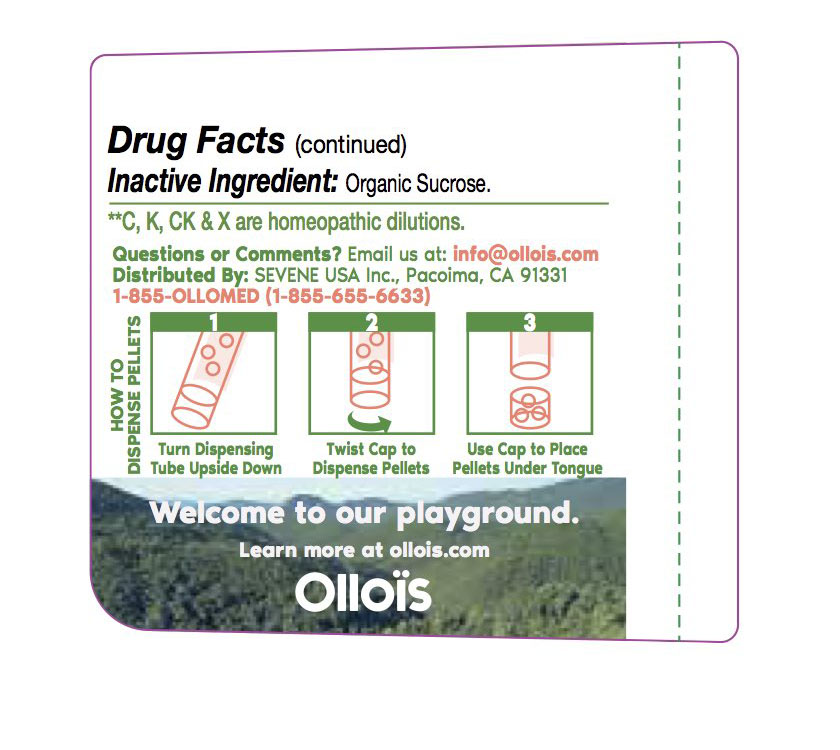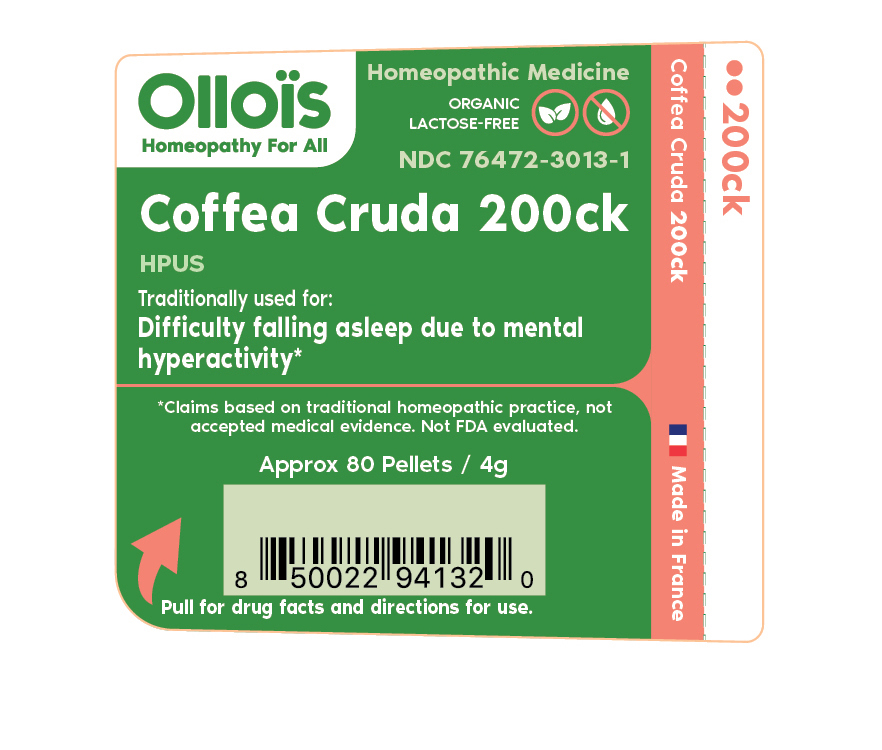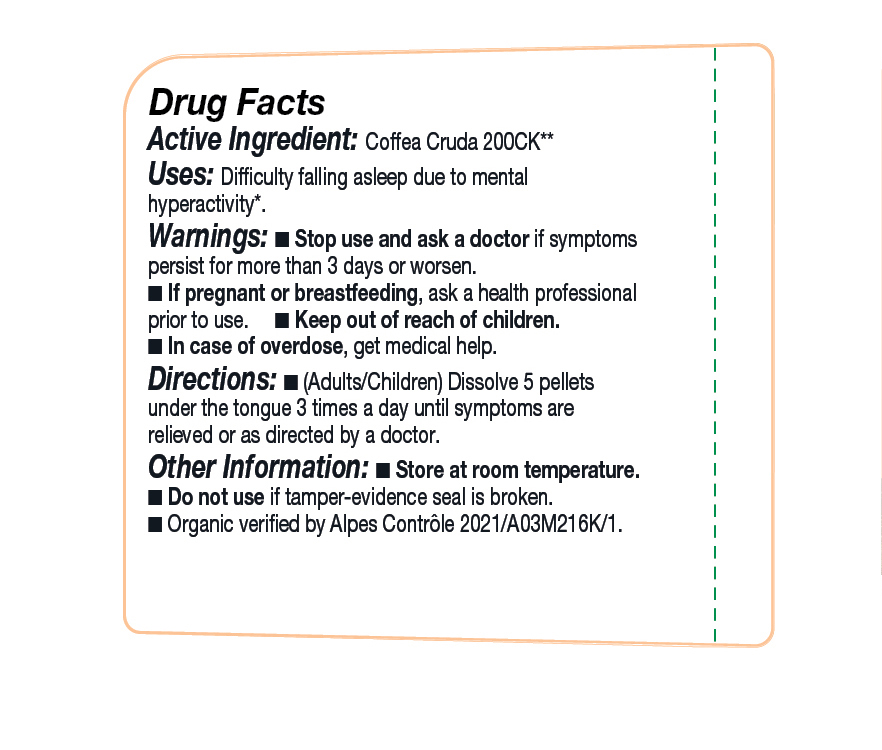 DRUG LABEL: Coffea Cruda

NDC: 76472-3013 | Form: PELLET
Manufacturer: SEVENE USA
Category: homeopathic | Type: HUMAN OTC DRUG LABEL
Date: 20250211

ACTIVE INGREDIENTS: ARABICA COFFEE BEAN 200 [kp_C]/1 1
INACTIVE INGREDIENTS: SUCROSE

Sevene USA (as PLD) - COFFEA CRUDA 200ck (76472-3013)

ACTIVE INGREDIENT:

Homeopathic dilution of HPUS Coffea Cruda 200ck **C, K, CK, AND X, ARE HOMEOPATHIC DILUTIONS

TRADITIONALLY USED FOR:

Difficulty falling asleep due to mental hyperactivity*

DIRECTIONS:

(adults/children) Dissolve 5 pellets under the tongue 3 times a day until symptoms are relieved or as directed by a physician.

USE:

Condition listed above or as directed by a physician.

WARNINGS:

Stop use and ask a physician if symptoms persist for more than 3 days or worsen.

PREGNANCY OR BREAST FEEDING

If pregnant or breast-feeding, ask a health professional before use.

Keep out of reach of children.

OTHER INFORMATION:

Store at room temperature.

Do not use if pellet-dispenser seal is broken.

INACTIVE INGREDIENT:

Sucrose.

QUESTIONS?

info@ollois.com * www.ollois.com * Made in France. Not reviewed by FDA and not guaranteed to be effective. This Homeopathic dilution may not be suseptible to scientific measurement.

USE:

Condition listed above or as directed by a physician.